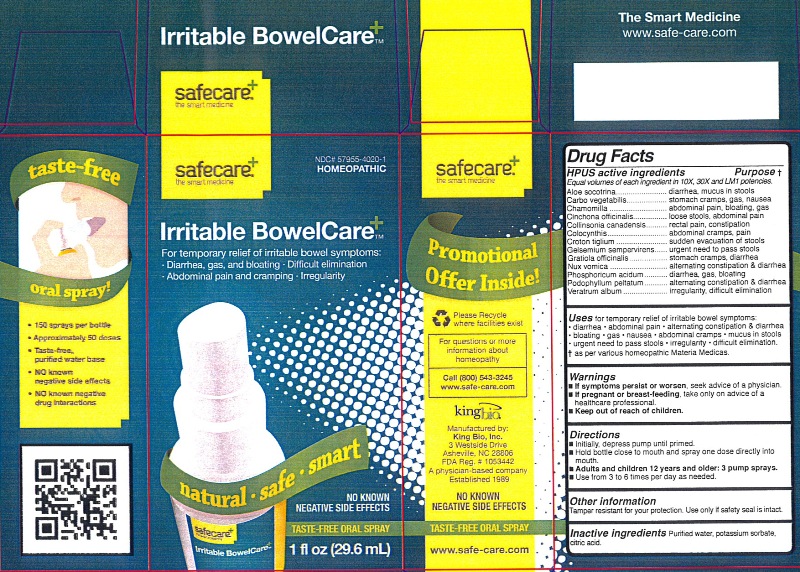 DRUG LABEL: Irritable BowelCare
NDC: 57955-4020 | Form: LIQUID
Manufacturer: King Bio Inc.
Category: homeopathic | Type: HUMAN OTC DRUG LABEL
Date: 20120613

ACTIVE INGREDIENTS: ALOE 10 [hp_X]/29.6 mL; ACTIVATED CHARCOAL 10 [hp_X]/29.6 mL; MATRICARIA RECUTITA 10 [hp_X]/29.6 mL; CINCHONA OFFICINALIS BARK 10 [hp_X]/29.6 mL; COLLINSONIA CANADENSIS ROOT 10 [hp_X]/29.6 mL; CITRULLUS COLOCYNTHIS FRUIT PULP 10 [hp_X]/29.6 mL; CROTON TIGLIUM SEED 10 mL/29.6 mL; GELSEMIUM SEMPERVIRENS ROOT 10 [hp_X]/29.6 mL; GRATIOLA OFFICINALIS 10 [hp_X]/29.6 mL; STRYCHNOS NUX-VOMICA SEED 10 [hp_X]/29.6 mL; PHOSPHORIC ACID 10 [hp_X]/29.6 mL; PODOPHYLLUM 10 [hp_X]/29.6 mL; VERATRUM ALBUM ROOT 10 [hp_X]/29.6 mL
INACTIVE INGREDIENTS: WATER; POTASSIUM SORBATE; CITRIC ACID MONOHYDRATE

Irritable BowelCare

Active Ingredients

HPUS active ingredients
Equal volumes of each ingredient in 10X, 30X and LM1 potencies.
Aloe socotrina, Carbo vegetabilis, Chamomilla, Cinchona officinalis, Collinsonia canadensis, Colocynthis, Croton tiglium, Gelsemium sempervirens, Gratiola officinalis, Nux vomica,Phosphoricum acidum, Podophyllum peltatum and Veratrum album.
Reference image bowelcare.jpg

Inactive Ingredients

Purified water, Potassium sorbate and citric acid.

Reference image bowelcare.jpg

Purpose

HPUS active ingredients Purpose
Equal volumes of each ingredient in 10X, 30X and LM1 potencies.
Aloe socotrina...............................................................diarrhea, mucus in stools
Carbo vegetabilis...........................................................stomach cramps, gas, nausea
Chamomilla...................................................................abdominal pain, bloating, gas
Cinchona officinalis........................................................loose stools, abdominal pain
Collinsonia canadensis...................................................rectal pain, constipation
Colocynthis...................................................................abdominal cramps, pain
Croton tiglium................................................................sudden evacuation of stools
Gelsemium sempervirens...............................................urgent need to pass stools
Gratiola officinalis..........................................................stomach cramps, diarrhea
Nux Vomica..................................................................alternating constipation and diarrhea
Phosphoricum acidum...................................................diarrhea, gas, bloating
Podophyllum peltatum....................................................alternating constipation and diarrhea
Veratrum album.............................................................irregularity, difficult elimination
Reference image bowelcare.jpg

Indications and Usage

Uses for temporary relief of irritable bowel symptoms:

- diarrhea
- abdominal pain
- alternating constipation and diarrhea
- bloating
- gas
- nausea
- abdominal cramps
- mucus in stools
- urgent need to pass stools
- irregularity
- difficult elimination

as per various homeopathic Materia Medicas.

Warnings

- If symptoms persist or worsen, seek advice of a physician.
- If pregnant or breast-feeding, take only on advice of a healthcare professional.
- Keep out of reach of children.

Other information
Tamper resistant for your protection. Use only if safety seal is intact.
Reference image bowelcare.jpg

Keep out of reach of children.

Dosage and Administration

Directions

- Initially, depress pump until primed.
- Hold bottle close to mouth and spray one dose directly into mouth
- Adults and children 12 years and older:3 pumps sprays.
- Use from 3 to 6 times per day as needed.

Reference image bowelcare.jpg

PACKAGE LABEL

King Bio, Inc.

3 Westside Drive

Asheville, NC 28806

For questions or more information about homeopathy call 800-543-3245 or www.safe-care.com